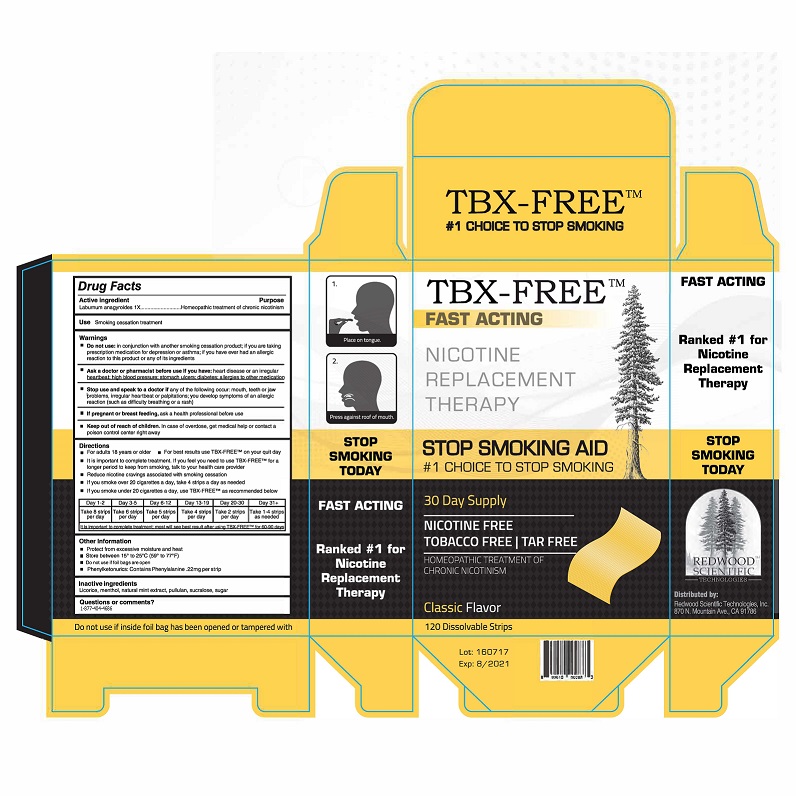 DRUG LABEL: TBX-Free
NDC: 72041-001 | Form: STRIP
Manufacturer: Dalian Holyone Bio-Technologyco Ltd
Category: homeopathic | Type: HUMAN OTC DRUG LABEL
Date: 20180119

ACTIVE INGREDIENTS: LABURNUM ANAGYROIDES POLLEN 1 [hp_X]/1 1
INACTIVE INGREDIENTS: MINT; SUCRALOSE; MENTHOL; SUCROSE; PULLULAN; LICORICE

TBX-Free

Active ingredient - Laburnum anagyroides 1x

PURPOSE

Homeopathic treatment of chronic nicothism

DOSAGE AND ADMINISTRATION

Directions and Use

- For adults 18 years or older
- For best results use TBX-FREE on your quit day
- It is important to complete treatment. If you feel you need to use TBX-FREE for a longer period to keep from smoking, talk to your health care provider.
- Reduce nicotine cravings associated with smoking cessation
- If you smoke over 20 cigarettes a day, take 4 strips a day as needed
- If you smoke under 20 cigarettes a day, use TBX-FREE as recommended below.

Do not use: In conjunction with another smoking cessation product; if you are taking prescription medication for depression or asthma; If you are taking prescription medication for depression or asthma; If you have ever had an allergic reaction to this product or any of its ingredients

Ask doctor of pharmacist before use if you have: heart disease or an irregular hearbeat; high blood pressure; stomach ulcers; diabetes; allergies to other medications

Stop use and speak to a doctor: If any of the following occur - mouth, teeth or jaw problems, irregular heartbeat or palpitations, you develop symptoms of an allergic reaction (such as difficulty breathing or a rash.

If pregnant or breast feeding, ask a health professional before use

Keep out of reach of children. In case of overdose, get medical help or contact a poison control center right away.

Keep out of reach of children. In case of overdose, get medical help or contact a poison control center right away

INDICATIONS AND USAGE

Smoking cessation treatment

INACTIVE INGREDIENTS

Licorice, menthol, natural mint extract, pullulan, sucralose, sugar